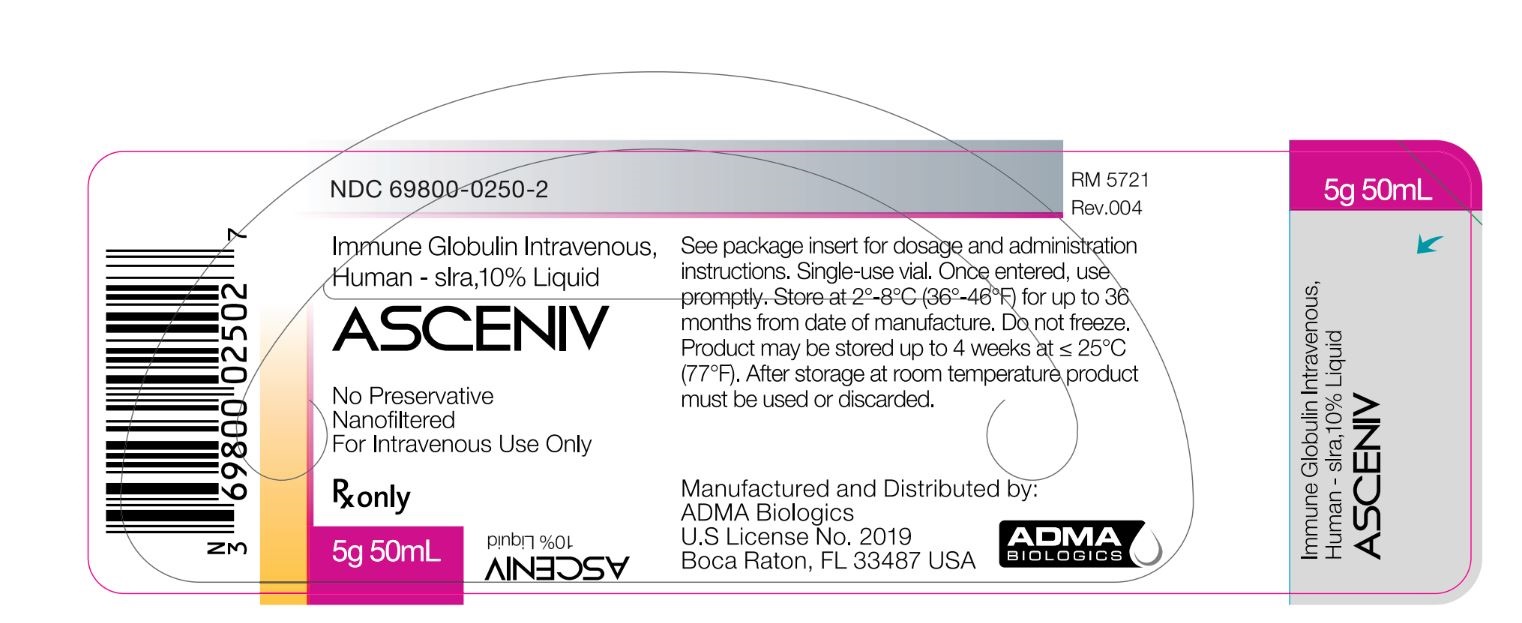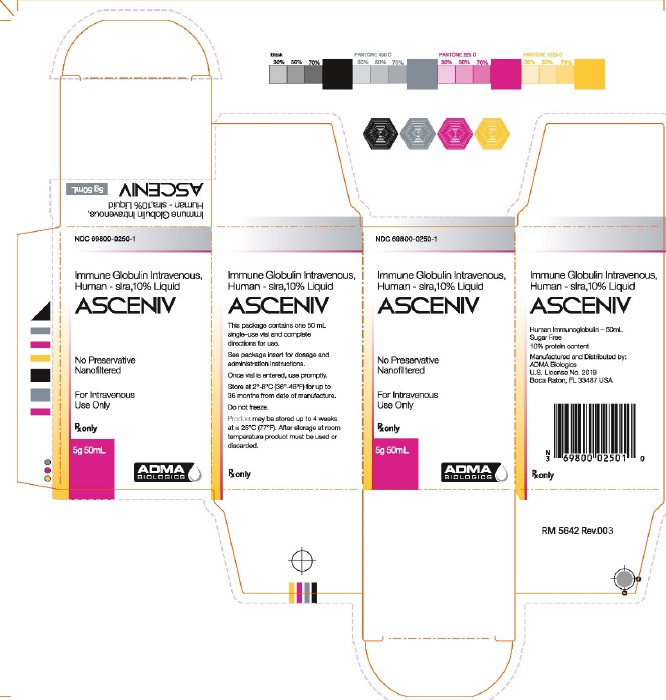 DRUG LABEL: ASCENIV
NDC: 69800-0250 | Form: LIQUID
Manufacturer: ADMA Biologics, Inc.
Category: prescription | Type: HUMAN PRESCRIPTION DRUG LABEL
Date: 20250506

ACTIVE INGREDIENTS: HUMAN IMMUNOGLOBULIN G 5 g/50 mL
INACTIVE INGREDIENTS: GLYCINE; SODIUM CHLORIDE; POLYSORBATE 80; WATER O-18

HIGHLIGHTS OF PRESCRIBING INFORMATION

These highlights do not include all the information needed to use ASCENIV™ safely and effectively.
See full prescribing information for ASCENIV.
ASCENIV (immune globulin intravenous, human – slra)
10% Liquid
Initial U.S. Approval: 2019

WARNING: THROMBOSIS, RENAL DYSFUNCTION AND ACUTE RENAL FAILURE

See full prescribing information for complete boxed warning.

- Thrombosis may occur with immune globulin intravenous (IGIV) products, including ASCENIV. Risk factors may include: advanced age, prolonged immobilization, hypercoagulable conditions, history of venous or arterial thrombosis, use of estrogens, indwelling vascular catheters, hyperviscosity, and cardiovascular risk factors.
- Renal dysfunction, acute renal failure, osmotic nephrosis, and death may occur with the administration of IGIV products in predisposed patients.
- Renal dysfunction and acute renal failure occur more commonly in patients receiving IGIV products containing sucrose. ASCENIV does not contain sucrose. [5.3]
- For patients at risk of thrombosis, renal dysfunction or renal failure, administer ASCENIV at the minimum dose and infusion rate practicable. Ensure adequate hydration in patients before administration. Monitor for signs and symptoms of thrombosis and assess blood viscosity in patients at risk for hyperviscosity. [2.1, 2.3, 5.3]

1 INDICATIONS AND USAGE

ASCENIV (immune globulin intravenous, human – slra) is a 10% immune globulin liquid for intravenous injection, indicated for the treatment of primary humoral immunodeficiency (PI) in adults and adolescents (12 to 17 years of age). [1]

2 DOSAGE AND ADMINISTRATION

For intravenous use only.

Dose | Initial Infusion Rate | Maintenance Infusion Rate (if tolerated)
300-800 mg/kg every 3- 4 weeks | 0.5 mg/kg/min (0.005 mL/kg/min) for the first 15 minutes | Increase gradually every 15 minutes (if tolerated) up to 8 mg/kg/min (0.08 mL/kg/min)

- Ensure that patients with pre-existing renal insufficiency are not volume depleted; discontinue ASCENIV if renal function deteriorates. [5.3]
- For patients at risk of renal dysfunction or thrombotic events, administer ASCENIV at the minimum infusion rate practicable. [5.2, 5.3]

3 DOSAGE FORMS AND STRENGTHS

ASCENIV is a liquid solution containing 10% IgG (100 mg/mL) for intravenous infusion; (5g in 50 mL solution). [3]

4 CONTRAINDICATIONS

- History of anaphylactic or severe systemic reactions to human immunoglobulin. [4]
- IgA-deficient patients with antibodies to IgA and a history of hypersensitivity. [4, 5.1]

5 WARNINGS AND PRECAUTIONS

- IgA-deficient patients with antibodies against IgA are at greater risk of developing severe hypersensitivity and anaphylactic reactions. Have medications such as epinephrine available to treat any acute severe hypersensitivity reactions. [4, 5.1]
- Thrombotic events have occurred in patients receiving IGIV treatments. Monitor patients with known risk factors for thrombotic events; consider baseline assessment of blood viscosity for patients at risk of hyperviscosity. [5.2, 5.4]
- In patients at risk of developing acute renal failure. monitor renal function, including blood urea nitrogen (BUN), serum creatinine, and urine output. [5.3, 5.9]
- Hyperproteinemia, increased serum viscosity, and hyponatremia or pseudohyponatremia can occur in patients receiving IGIV treatment. [5.4]
- Aseptic meningitis syndrome (AMS) has been reported with IGIV treatments, especially with high doses or rapid infusion. [5.5]
- Hemolytic anemia can develop subsequent to IGIV treatment. Monitor patients for hemolysis and hemolytic anemia. [5.6]
- Monitor patients for pulmonary adverse reactions (Transfusion-related acute lung injury [TRALI]). If transfusion-related acute lung injury is suspected, test the product and patient for antineutrophil antibodies. [5.7]
- Because this product is made from human blood, it may carry a risk of transmitting infectious agents, e.g., viruses, and theoretically, the Creutzfeldt-Jakob disease (CJD) agent. [5.8]

6 ADVERSE REACTIONS

The most common adverse reactions to ASCENIV (≥5% of study subjects) were headache, sinusitis, diarrhea, gastroenteritis viral, nasopharyngitis, upper respiratory tract infection, bronchitis, and nausea. [6]

To report SUSPECTED ADVERSE REACTIONS, contact ADMA Biologics at (1-800-458-4244) or FDA at 1-800-FDA-1088 or www.fda.gov/medwatch.

7 DRUG INTERACTIONS

- Passive transfer of antibodies may transiently interfere with the immune response to live virus vaccines, such as measles, mumps, rubella, and varicella. [7]
- Passive transfer of antibodies may confound the results of serological testing. [5.10]

8 USE IN SPECIFIC POPULATIONS

Geriatric Use: In patients over age 65 or in any patient at risk of developing renal insufficiency, do not exceed the recommended dose, and infuse ASCENIV at the minimum infusion rate practicable. [8.5]

FULL PRESCRIBING INFORMATION

WARNING: THROMBOSIS, RENAL DYSFUNCTION AND ACUTE RENAL FAILURE

- Thrombosis may occur with immune globulin (IGIV) products, including ASCENIV. Risk factors may include: advanced age, prolonged immobilization, hypercoagulable conditions, history of venous or arterial thrombosis, use of estrogens, indwelling central vascular catheters, hyperviscosity, and cardiovascular risk factors. Thrombosis may occur in the absence of known risk factors (see Warnings and Precautions [5.2], Patient Counseling Information [17]).
- Renal dysfunction, acute renal failure, osmotic nephrosis, and death may occur with the administration of IGIV products in predisposed patients.
- Renal dysfunction and acute renal failure occur more commonly in patients receiving IGIV products containing sucrose. ASCENIV does not contain sucrose.
- For patients at risk of thrombosis, renal dysfunction or renal failure, administer ASCENIV at the minimum dose and infusion rate practicable. Ensure adequate hydration in patients before administration. Monitor for signs and symptoms of thrombosis and assess blood viscosity in patients at risk for hyperviscosity (see Dosage and Administration [2.1, 2.3], Warnings and Precautions [5.3]).

1 INDICATIONS AND USAGE

ASCENIV (immune globulin intravenous, human – slra) is a 10% immune globulin liquid for intravenous injection, indicated for the treatment of primary humoral immunodeficiency (PI) in adults and adolescents (12 to 17 years of age). PI includes, but is not limited to, the humoral immune defect in congenital agammaglobulinemia, common variable immunodeficiency (CVID), X-linked agammaglobulinemia, Wiskott-Aldrich syndrome, and severe combined immunodeficiencies (SCID).

2 DOSAGE AND ADMINISTRATION

2.1 Dose

The recommended dose of ASCENIV for replacement therapy in primary humoral immunodeficiency (PI) is 300 to 800 mg/kg body weight administered every 3 to 4 weeks. The dose may be adjusted over time to achieve the desired trough levels and clinical response.

ASCENIV dose adjustments may be required in patients who fail to maintain trough total IgG concentrations of at least 500 mg/ dL with a target of 600 mg/dL. Starting with the second infusion, adjust the dose proportionally, targeting a trough of ≥ 600 mg/dL, based on the previous trough and the associated dose.

For intravenous use only.

Table 1
Dose | Initial Infusion Rate | Maintenance Infusion Rate (if tolerated)
300-800 mg/kg every 3-4 weeks | 0.5 mg/kg/min (0.005 mL/kg/min) for the first 15 minutes | Increase gradually every 15 minutes (if tolerated) up to 8 mg/kg/min (0.08 mL/kg/min)

2.2 Preparation and Handling

- ASCENIV is a clear to opalescent, colorless to pale yellow solution. Inspect visually for particulate matter and discoloration prior to administration. Do not use if the liquid is cloudy or turbid, or if it contains visible particulate matter.
- Allow refrigerated product to come to room temperature before use and maintain ASCENIV at room temperature during administration.
- DO NOT MICROWAVE.
- DO NOT SHAKE.
- DO NOT MIX with other IGIV products or other intravenous medications.
- DO NOT DILUTE.
- ASCENIV contains no preservatives. Each vial is for single use only. Do not reuse or save for future use.
- If large doses are required, several vials may be pooled using aseptic technique into sterile infusion bags and infused.

2.3 Administration

Begin with an initial infusion rate of 0.5 mg/kg/min. If there are no adverse reactions, the infusion rate for subsequent infusions can be slowly increased to the maximum rate.

Monitor patient vital signs throughout the infusion. Slow or stop the infusion if adverse reactions occur. If symptoms subside promptly, the infusion may be resumed at a slower rate which is comfortable for the patient.

Ensure that patients with pre-existing renal insufficiency are not volume-depleted. For patients judged to be at risk for renal dysfunction or thrombotic events, administer ASCENIV at the minimum infusion rate practicable, and consider discontinuation of administration if renal function deteriorates (see Boxed Warning, Warnings and Precautions [5.2, 5.3]).

3 DOSAGE FORMS AND STRENGTHS

ASCENIV is a liquid solution containing 10% IgG (100 mg/mL) for intravenous infusion.

4 CONTRAINDICATIONS

ASCENIV is contraindicated in:

- patients who have had an anaphylactic or severe systemic reaction to the administration of human immune globulin.
- IgA-deficiency patients with antibodies to IgA and a history of hypersensitivity.

5 WARNINGS AND PRECAUTIONS

5.1 Hypersensitivity

Severe hypersensitivity reactions may occur with IGIV products, including ASCENIV. In case of hypersensitivity, discontinue ASCENIV infusion immediately and institute appropriate treatment. Medications such as epinephrine should be available for treatment of acute hypersensitivity reactions.

ASCENIV contains trace amounts of IgA (≤ 200 micrograms per milliliter) (see Description [11]). Patients with known antibodies to IgA may have a greater risk of developing potentially severe hypersensitivity and anaphylactic reactions. ASCENIV is contraindicated in IgA-deficient patients with antibodies against IgA and a history of hypersensitivity reaction (see Contraindications [4]).

5.2 Thrombosis

Thrombosis may occur following treatment with immune globulin products, including ASCENIV.^4,5,6 Risk factors may include: advanced age, prolonged immobilization, hypercoagulable conditions, history of venous or arterial thrombosis, use of estrogens, indwelling central vascular catheters, hyperviscosity and cardiovascular risk factors. Thrombosis may occur in the absence of known risk factors.

Consider baseline assessment of blood viscosity in patients at risk for hyperviscosity, including patients with cryoglobulins, fasting chylomicronemia/markedly high triacylglycerols (triglycerides), or monoclonal gammopathies. For patients at risk of thrombosis, administer ASCENIV at the minimum dose and infusion rate practicable. Ensure adequate hydration in patients before administration. Monitor for signs and symptoms of thrombosis and assess blood viscosity in patients at risk for hyperviscosity (see Boxed Warning, Dosage and Administration [2], Patient Counseling Information [17]).

5.3 Acute Renal Dysfunction and Acute Renal Failure

Acute renal dysfunction/failure, osmotic nephrosis, and death^1,2 may occur upon use of human IGIV products. Ensure that patients are not volume depleted before administering ASCENIV. Periodic monitoring of renal function and urine output is particularly important in patients judged to be at increased risk of developing acute renal failure.^2 Assess renal function, including measurement of blood urea nitrogen (BUN) and serum creatinine, before the initial infusion of ASCENIV and at appropriate intervals thereafter. If renal function deteriorates, consider discontinuing ASCENIV (see Patient Counseling Information [17]). In patients who are at risk of developing renal dysfunction, because of pre-existing renal insufficiency or predisposition to acute renal failure (such as diabetes mellitus, hypovolemia, overweight, use of concomitant nephrotoxic medicinal products or age of >65 years), administer ASCENIV at the minimum infusion rate practicable (see Dosage and Administration [2]).

5.4 Hyperproteinemia, Increased Serum Viscosity, and Hyponatremia

Hyperproteinemia, increased serum viscosity, and hyponatremia may occur in patients receiving IGIV treatment, including ASCENIV. It is critical to clinically distinguish true hyponatremia from a pseudohyponatremia that is associated with or causally related to hyperproteinemia with concomitant decreased calculated serum osmolality or elevated osmolar gap, because treatment aimed at decreasing serum free water in patients with pseudohyponatremia may lead to volume depletion, a further increase in serum viscosity, and a possible predisposition to thrombotic events.^3

5.5 Aseptic Meningitis Syndrome (AMS)

AMS may occur with IGIV treatments, including ASCENIV. AMS usually begins within several hours to 2 days following IGIV treatment. Discontinuation of IGIV treatment has resulted in remission of AMS within several days without sequelae.^7,8,9

AMS may occur more frequently in association with high doses (2 g/kg) and/or rapid infusion of IGIV.

AMS is characterized by the following signs and symptoms: severe headache, nuchal rigidity, drowsiness, fever, photophobia, painful eye movements, nausea, and vomiting (see Patient Counseling Information [17]). Cerebrospinal fluid (CSF) studies frequently reveal pleocytosis up to several thousand cells per cubic millimeter, predominantly from the granulocytic series, and elevated protein levels up to several hundred mg/dL, but negative culture results. Conduct a thorough neurological examination on patients exhibiting such signs and symptoms, including CSF studies, to rule out other causes of meningitis.

5.6 Hemolysis

IGIV products, including ASCENIV, may contain blood group antibodies that can act as hemolysins and induce in vivo coating of red blood cells (RBCs) with immunoglobulin, causing a positive direct antiglobulin reaction and hemolysis.^10,11,12 Delayed hemolytic anemia can develop subsequent to IGIV treatment due to enhanced RBC sequestration,^13 and acute hemolysis, consistent with intravascular hemolysis, has been reported.

Monitor patients for clinical signs and symptoms of hemolysis (see Patient Counseling Information [17]). If these are present after ASCENIV infusion, perform appropriate confirmatory laboratory testing. If transfusion is indicated for patients who develop hemolysis with clinically compromising anemia after receiving IGIV, perform adequate cross-matching to avoid exacerbating ongoing hemolysis.

5.7 Transfusion-Related Acute Lung Injury (TRALI)

Noncardiogenic pulmonary edema may occur in patients following IGIV treatment,^14 including ASCENIV. TRALI is characterized by severe respiratory distress, pulmonary edema, hypoxemia, normal left ventricular function, and fever. Symptoms typically appear within 1 to 6 hours following treatment.

Monitor patients for pulmonary adverse reactions. If TRALI is suspected, perform appropriate tests for the presence of anti-neutrophil antibodies in both the product and the patient’s serum (see Patient Counseling Information [17]).

TRALI may be managed using oxygen therapy with adequate ventilatory support.

5.8 Transmissible Infectious Agents

Because ASCENIV is made from human blood, it may carry a risk of transmitting infectious agents, e.g., viruses, the variant Creutzfeldt-Jakob disease (vCJD) and theoretically, the Creutzfeldt-Jakob disease (CJD) agent.

All infections suspected by a physician possibly to have been transmitted by this product should be reported by the physician or other healthcare provider to ADMA Biologics at (1-800-458-4244). Before prescribing ASCENIV, the physician should discuss the risks and benefits of its use with the patient (see Patient Counseling Information [17]).

5.9 Monitoring Laboratory Tests

- Periodic monitoring of renal function and urine output is particularly important in patients at increased risk of developing acute renal failure. Assess renal function, including measurement of blood urea nitrogen (BUN) and serum creatinine, before the initial infusion of ASCENIV and at appropriate intervals thereafter.
- Because of the potentially increased risk of thrombosis with IGIV treatment, consider baseline assessment of blood viscosity in patients at risk for hyperviscosity, including those with cryoglobulins, fasting chylomicronemia/markedly high triacylglycerols (triglycerides), or monoclonal gammopathies.
- If signs and/or symptoms of hemolysis are present after an infusion of ASCENIV, perform appropriate laboratory testing for confirmation.
- If TRALI is suspected, perform appropriate tests for the presence of anti-neutrophil antibodies in both the product and patient’s serum.

5.10 Interference with Laboratory Tests

After infusion of immunoglobulin, the transitory rise of the various passively transferred antibodies in the patient’s blood may yield positive serological testing results, with the potential for misleading interpretation. Passive transmission of antibodies to erythrocyte antigens (e.g., A, B, and D) may cause a positive direct or indirect antiglobulin (Coombs’) test.

6 ADVERSE REACTIONS

The most common adverse reactions to ASCENIV (reported in ≥5% of clinical study subjects) were headache, sinusitis, diarrhea, gastroenteritis viral, nasopharyngitis, upper respiratory tract infection, bronchitis, and nausea.

6.1 Clinical Trials Experience

Because clinical trials are conducted under widely varying conditions, adverse reaction rates observed in clinical trials cannot be directly compared to rates in the clinical trials of another product and may not reflect the rates observed in clinical practice.

In a multicenter, open-label, non-randomized clinical trial, 59 subjects with PI, on regular IGIV replacement therapy, received doses of ASCENIV ranging from 284 to 1008 mg/kg (mean dose 505 mg/kg) every 3 weeks or 4 weeks for up to 12 months (mean 346 days; range 36 to 385 days) (see Clinical Studies [14]). The use of pre-medication was discouraged; however, if after two infusions of ASCENIV subjects required pre-medication (antipyretic, antihistamine, or antiemetic agent) for recurrent reactions, they could continue those medications for the duration of the trial. Of the 793 infusions administered during this trial, only 7 (11.9%) subjects received premedication prior to 7 (0.9%) infusions.

Fifty-eight subjects (98%) had an adverse reaction during the study. The proportion of subjects who had at least one adverse reaction was similar for both the 3- and 4-week cycles. The most common adverse reactions observed in this clinical trial were headache (22 subjects, 37%), sinusitis (16 subjects, 27%), diarrhea (14 subjects, 23%), gastroenteritis viral (13 subjects, 22%), nasopharyngitis (13 subjects, 22%), upper respiratory tract infection (13 subjects, 22%), bronchitis (12 subjects, 20%), nausea (12 subjects, 20%), and acute sinusitis (11 subjects, 19%).

Adverse reactions (ARs) occurring during or within 72 hours after the end of an infusion are presented in Table 2. In this study, the upper bound of the 1-sided 95% confidence interval for the proportion of ASCENIV infusions with one or more temporally associated adverse reactions was 16.4%. The total number of adverse reactions was 158 (a rate of 0.20 ARs per infusion).

Table 2: Adverse Reactions (ARs) (within 72 hours after the end of an ASCENIV infusion) in ≥ 5% of Subjects
Preferred Term (MedDRA v16.0) | Number (%) of Subjects (N=59) | Number (%) of Infusions (N=793)
Headache | 14 (24) | 21 (2.6)
Sinusitis | 6 (10) | 7 (0.9)
Nausea | 5 (9) | 5 (0.6)
Acute sinusitis | 4 (7) | 4 (0.5)
Fatigue | 4 (7) | 9 (1.1)
Muscle spasms | 4 (7) | 4 (0.5)
Bronchitis | 3 (5) | 3 (0.4)
Diarrhea | 3 (5) | 3 (0.4)
Nose Bleed | 3 (5) | 4 (0.5)
Muscle Pain | 3 (5) | 5 (0.6)
Oropharyngeal pain | 3 (5) | 3 (0.4)
Pain in extremity | 3 (5) | 3 (0.4)
Itching | 3 (5) | 3 (0.4)

6.2 Postmarketing Experience

Because postmarketing reporting of adverse reactions is voluntary and from a population of uncertain size, it is not always possible to reliably estimate the frequency of these reactions or establish a causal relationship to product exposure. The following adverse reactions have been identified and reported during the post-approval use of IGIV products:

- Respiratory: Apnea, Acute Respiratory Distress Syndrome (ARDS), cyanosis, dyspnea, bronchospasm.
- Cardiovascular: Cardiac arrest, vascular collapse, hypotension.
- Neurological: Coma, loss of consciousness, seizures, tremor.
- Integumentary: Stevens-Johnson syndrome, epidermolysis, erythema multiforme, bullous dermatitis.
- Hematologic: Pancytopenia, leukopenia.
- General/Body as a Whole: Pyrexia, rigors.
- Gastrointestinal: Hepatic dysfunction, abdominal pain.

7 DRUG INTERACTIONS

Immunoglobulin administration may transiently impair the efficacy of live attenuated virus vaccines such as measles, mumps, rubella, and varicella because the continued presence of high levels of passively acquired antibody may interfere with an active antibody response.^15,16 The immunizing physician should be informed of recent therapy with ASCENIV so that appropriate measures may be taken (see Patient Counseling Information [17]).

8 USE IN SPECIFIC POPULATIONS

8.1 Pregnancy

Risk Summary

No human data are available to indicate the presence or absence of drug-associated risk. Animal reproduction studies have not been conducted with ASCENIV. It is not known whether ASCENIV can cause fetal harm when administered to a pregnant woman or can affect reproduction capacity. Immune globulins cross the placenta from maternal circulation increasingly after 30 weeks of gestation. In the U.S. general population, the estimated background risk of major birth defects and miscarriage in clinically recognized pregnancies is 2-4% and 15-20% respectively. ASCENIV should be given to pregnant women only if clearly needed.^17,18

8.2 Lactation

Risk Summary

No human data are available to indicate the presence or absence drug-associated risk. The developmental and health benefits of breast feeding should be considered along with the mother’s clinical need for ASCENIV and any potential adverse effects on the breast-fed infant from ASCENIV or from the underlying maternal condition.

8.4 Pediatric Use

ASCENIV was evaluated in 11 pediatric subjects (6 children less than 12 years and 5 adolescents age 12 – 16 years) with primary humoral immunodeficiency (PI). The pharmacokinetic (PK), safety, and effectiveness profile of ASCENIV in adolescent subjects appeared to be comparable to that demonstrated in adult subjects. There are insufficient PK, safety, and effectiveness data from pediatric subjects younger than 12 years. Safety and effectiveness has not been studied in pediatric patients with PI who are under the age of 3 years (see Clinical Studies [14]).

8.5 Geriatric Use

Clinical studies of ASCENIV did not include sufficient numbers of subjects aged 65 and over to determine whether they respond differently from younger subjects. Other reported clinical experience has not identified differences in responses between the elderly and younger patients. In general, dose selection for an elderly patient should be cautious, usually starting at the low end of the dosing range, reflecting the greater frequency of decreased hepatic, renal, or cardiac function, and of concomitant disease or other drug therapy.

10 OVERDOSAGE

With intravenous administration, overdose may lead to fluid overload and hyperviscosity. Patients at risk of complications of fluid overload and hyperviscosity include elderly patients and those with cardiac or renal impairment.

11 DESCRIPTION

ASCENIV is a purified, sterile, ready-to-use preparation of concentrated human immunoglobulin G (IgG) antibodies. The distribution of IgG subclasses is similar to that of normal plasma. The active ingredient is human immunoglobulin purified from source human plasma and processed using a modified classical Cohn Method 6 / Oncley Method 9 fractionation process as well as anion and cation exchange steps for added purification. ASCENIV contains 100 ± 10 mg/mL protein, of which not less than 96% is human immunoglobulin obtained from source human plasma. It is formulated in water for injection containing 0.100-0.140 M sodium chloride, 0.20-0.29 M glycine, 0.15–0.25% polysorbate 80, and pH 4.0–4.6. ASCENIV contains ≤ 200 µg/mL of IgA.

Each plasma donation used for the manufacture of ASCENIV is collected from FDA-licensed facilities and undergoes rigorous testing. Plasma donations must test negative for hepatitis B virus (HBV) surface antigen (HBsAg), antibodies to human immunodeficiency virus (HIV) strains 1 and 2 (anti-HIV-1/2), and antibodies to the hepatitis C virus (anti-HCV) as determined by enzyme immune assay (EIA). In addition, each plasma unit must test negative and/or non-reactive for HIV RNA, HCV RNA, HBV DNA, Hepatitis A Virus (HAV) RNA, and Parvovirus B19 (B19 virus) DNA as determined by Nucleic Acid Amplification Testing (NAT) of plasma minipools. NAT is also performed on a sample of the manufacturing pool and must be negative and/or non-reactive for HIV RNA, HCV RNA, HBV DNA, and Hepatatis A Virus (HAV) RNA, and the limit for B19 virus DNA in a manufacturing pool is set not to exceed 10^4 IU/mL.

The manufacturing process of ASCENIV employs six steps to remove/inactivate adventitious viruses to minimize the risk of virus transmission. The steps are "Precipitation and removal of fraction III" during cold ethanol fractionation, "Q-membrane filtration", "Solvent/detergent treatment" (TnBP / Triton X-100), "Anion exchange chromatography" and "virus filtration". In compliance with current guidelines, the steps have been separately validated in a series of in vitro experiments for their capacity to inactivate or remove both enveloped and non-enveloped viruses.

Precipitation and removal of fraction III and Q-membrane filtration removes non-enveloped viruses, solvent/detergent treatment represents a virus inactivation step for enveloped viruses, Anion exchange chromatography binds enveloped and non-enveloped viruses, and virus filtration removes both enveloped and non-enveloped viruses by size exclusion. In addition to the steps above, low pH during several steps of the production process contributes to virus inactivation. The results of virus validation studies for the ASCENIV process are shown in Table 3, expressed as log10 reduction factors.

Table 3: Virus Validation Data for ASCENIV
Step/Virus | HIV | BVDV | SinV | WNV | PRV | MEV | EMC | BPV | PPV | SV40
Virus Type | Enveloped | Enveloped | Enveloped | Enveloped | Enveloped | Non-enveloped | Non-enveloped | Non-enveloped | Non-enveloped | Non-enveloped
Virus Family | Retro | Flavi | Flavi | Flavi | Herpes | Picorna | Picorna | Parvo | Parvo | Polyoma
Precipitation and Removal of Fraction III and Depth Filtration | - |  | - | - | - | 5.29 | ≥5.70 | - | ≥5.78 | 2.00*
Q-Membrane Filtration^1 | - | - | - | - | - | - | - | - | 2.02 | -
Solvent Detergent TNBP/Triton X-100 Treatment | ≥3.92 | ≥5.32 | >7.11 | >4.96 | ≥4.88 | - |  | - | - | -
Anion Exchange Chromatography | 1.04 | - | - | - | - | - | - | - | 1.09 | -
Virus Nanofiltration | ≥4.72 | ≥4.67 | - | - | ≥4.15 |  | ≥6.24 | 6.18 | 4.66 | >5.02
Low pH Treatment^2 | 2.43 | - | - | - | 3.20^2 | - | - | - | - | -
Total Clearance | ≥9.68 | ≥9.99 | > 7.11 | > 4.96 | ≥12.23 | 5.29 | ≥5.70^3 | 6.18 | 11.49 | > 7.02
* without depth filtration
HIV, human immunodeficiency virus; BVDV, Bovine viral diarrhea virus, model virus for HCV; SinV, Sindbis virus, model virus for HCV; WNV, West Nile virus; PRV, Pseudorabies virus, model virus for herpes viruses and Hepatitis B virus; MEV, Murine encephalomyelitis virus, model virus for hepatitis A virus; BPV, Bovine parvovirus, model virus for human B19 virus; PPV, Porcine parvovirus, model virus for human B19 virus; SV40, Simian virus 40, model virus for highly resistant non-enveloped viruses. EMC, Encephalomyocarditis virus, model virus for hepatitis A virus
1 Q-membrane filtration step is associated with the affinity stream part of the production process.
2 Low pH treatment included in total clearance calculation based on separate mode of inactivation than VRF.
3 EMC total clearance was calculated with the most conservative approach of using the lowest reduction value (>5.70) between the Fraction III precipitation/ filtration and nanofiltration steps.

12 CLINICAL PHARMACOLOGY

12.1 Mechanism of Action

ASCENIV is a replacement therapy for patients with primary humoral immunodeficiency (PI) (e.g. agammaglobulinemia, hypogammaglobulinemia, CVID, SCID).

The broad spectrum of neutralizing IgG antibodies against bacterial and viral pathogens and their toxins helps to avoid recurrent serious opportunistic infections. IgG antibodies are opsonins that increase phagocytosis and elimination of pathogens from the circulation. The mechanism of action has not been fully elucidated in PI.

12.2 Pharmacodynamics

ASCENIV contains mainly immunoglobulin G (IgG) with a broad spectrum of antibodies against various infectious agents, reflecting the IgG activity found in the donor population. ASCENIV which is prepared from pooled plasma from not less than 1,000 donors, has an IgG subclass distribution similar to that of native human plasma. Adequate doses of IGIV can restore an abnormally low IgG level to the normal range. Standard pharmacodynamics studies were not performed.

12.3 Pharmacokinetics

In a prospective, open-label, single-arm, multicenter clinical study, efficacy, safety and pharmacokinetics of ASCENIV were evaluated in 59 subjects with PI (See Clinical Studies [14]). Serum concentrations of total IgG were measured in 30 subjects (four subjects, ages 7 to 16 years and 26 subjects from 17 to 74 years) following the seventh infusion for subjects on a 4-week dosing interval and the ninth infusion for subjects on a 3-week dosing interval. The dose of ASCENIV used in these subjects ranged from 291 mg/kg to 760 mg/kg. After the infusion, blood samples were taken until Day 28 after infusion for the 4-week dosing interval and until Day 21 after infusion for the 3-week dosing interval. Table 4 summarizes the Total IgG Pharmacokinetic Parameters of ASCENIV, based on serum concentration of total IgG. The mean ± SD half-life of ASCENIV was 28.5 ± 4.4 days for subjects on a 3-week dosing interval and 39.7 ± 11.6 days for subjects on a 4-week dosing interval for the 30 subjects in the pharmacokinetic subgroup. Although no systematic study was conducted to evaluate the effect of sex on the pharmacokinetics of ASCENIV, based on the small sample size (11 males and 19 females) the pharmacokinetics of ASCENIV was comparable between males and females. In adolescents, the pharmacokinetics of ASCENIV was comparable with adults. There were insufficient PK data in children younger than 12 years.

Table 4: Total IgG Pharmacokinetic Parameter Estimates (PK Population) in Subjects
 | 3-week cycle (n = 10) |  | 4-week cycle (n = 20)
Statistic | Mean (SD) | CV% | Mean (SD) | CV%
Cmax (mg/dL) | 2,427 (452) | 18.6 | 2,227 (584) | 26.2
Cmin (mg/dL) | 1,152 (308) | 26.7 | 954 (245) | 25.7
Tmax (h)a | 2.93 (1.80, 4.52) | NA | 2.78 (1.43, 99.1) | NA
AUCtau (d*mg/dL) | 32,128 (7,020) | 21.9 | 35,905 (9,351) | 26.0
t½ (d) | 28.47 (4.4) | 15.4 | 39.70 (11.6) | 29.1
CL (mL/d/kg) | 1.68 (0.4) | 25.4 | 1.47 (0.5) | 33.6
Vss(mL/kg) | 76.79 (13.5) | 17.5 | 89.57 (26.2) | 29.2
AUCtau = steady-state area under the plasma concentration versus time curve with tau = dosing interval; CL = total body clearance; Cmax = maximum concentration; Cmin = minimum concentration;
CV = coefficient of variation; n = number of subjects; NA = not applicable; SD = standard deviation;
Tmax = time of maximum concentration; t½ = terminal half-life; Vss = Volume of distribution steady-state;a median (range)

Table 5: Total IgG Pharmacokinetic Parameter Estimates (PK Population) in Subjects—Baseline Corrected
 | 3-week cycle |  |  | 4-week cycle
Statistic | Mean (SD) | CV% | N | Mean (SD) | CV% | N
Cmax (mg/dL) | 1223 (297) | 24.2 | 10 | 1231 (453) | 37 | 20
Cmax (mg/dL) | 19 (31) | 166 | 10 | 46 (42) | 178 | 20
Tmax (h) | 3.04 (0.8) | 27 | 10 | 8 (22) | 282 | 20
AUC(0-t) (d*mg/dL) | 6604 (2913) | 44 | 10 | 7936 (3482) | 44 | 20
t½ (d) | 6 (2) | 41 | 5 | 10 (8) | 80 | 9
CL (mL/d/kg) | 9 (4) | 42 | 10 | 8 (5) | 61 | 20
Vz (mL/kg) | 82 (62) | 75 | 5 | 82 (35) | 43 | 9
AUC(0-t) = steady-state area under the plasma concentration versus time curve with 0-t = dosing interval; CL = total body clearance;
Cmax = maximum concentration;Cmin = minimum concentration; CV = coefficient of variation; N = number of subjects;
SD = standard deviation; Tmax = time of maximum concentration; t½ = terminal half-life;
Vz = Apparent Volume of distribution during terminal phase;

13 NONCLINICAL TOXICOLOGY

13.1 Carcinogenesis, Mutagenesis, Impairment of Fertility

No animal studies were conducted to evaluate the carcinogenic or mutagenic effects of ASCENIV or its effects on fertility.

13.2 Animal Toxicology and/or Pharmacology

No animal studies were conducted to evaluate possible toxicity of ASCENIV.

ASCENIV contains Polysorbate 80; Intravenous administrations of Polysorbate 80 in multiple species have been linked with a decrease in blood pressure. In rats, single doses of Polysorbate 80 that were up to 25 times higher than the amount from 800 mg/kg ASCENIV resulted in an increase of liver enzymes and total bilirubin.

14 CLINICAL STUDIES

A prospective, open-label, single-arm, multicenter trial assessed the efficacy, safety, and pharmacokinetics of ASCENIV in adult and pediatric subjects with PI. Study subjects were receiving regular IGIV replacement therapy, with a stable dose between 300 and 800 mg/kg for at least 3 months prior to participation in this trial. Subjects received an ASCENIV infusion administered every 3 or 4 weeks (both the dose and schedule depending on their prior therapy) for 12 months.

A total of 59 subjects were enrolled into the trial, 28 men and 31 women with a mean age of 42 years; 93% were Caucasian, 5% were Hispanic and 2% African American. Forty-eight subjects were adults (81%) between 17 and 74 years of age. There were 11 pediatric subjects (see Pediatric Use [8.4]), and 11 subjects (18.6%) ≥65 years of age. The oldest subject was 74 years of age. The youngest subject was 3 years of age.

There were 19 subjects with a 3-week cycle and 40 subjects with a 4-week cycle. There were 45 subjects (76%) with common variable immunodeficiency (CVID) as their primary diagnosis, followed by X-linked Agammaglobulinemia (10%), Antibody Deficiencies and ‘Other’ (7% each). The modified intent-to-treat (mITT) population included 59 subjects and was used for efficacy analysis.

The study assessed the efficacy of ASCENIV in preventing serious bacterial infections (SBIs), defined as a rate of <1.0 cases of bacterial pneumonia, bacteremia/septicemia, osteomyelitis/septic arthritis, visceral abscess, and bacterial meningitis per person-year. Secondary efficacy parameters included time to first SBI and time to first infection of any kind/seriousness, days on antibiotics (excluding prophylaxis), days off school/work due to infections, all confirmed infections of any kind or seriousness, and hospitalizations due to infection.

During the 12-month study period, zero (0) serious acute bacterial infections occurred. Thus, the mean event rate of serious, acute, bacterial infections per year was 0.0 (with an upper 1-sided 99% confidence interval of <1.0 per subject year, which met the study’s primary efficacy endpoint).

Thirty-nine percent (39%) of subjects had days off work, school or daycare due to an infection. Of the infections reported, 1 resulted in hospitalization as a post-op local wound infection from elective surgery (see Table 6). The incidence and severity of infections in adolescents were similar to those in adult subjects.

Table 6: Summary of Efficacy Results in Subjects with PI
Number of Subjects (mITT Population) Total Number of person-yearsa | 59 55.9
Infections Number of confirmed serious acute bacterial infectionsb Rate of SBIs (SBIs/total person-years) Rate of Infections (Infections/total person-years)a | 0 0.0 3.4
Antibiotic use due to infectionc Number of subjects (%) Days per subject per year | 37 (63%) 32.9
Days off school/daycare/work due to infection Number of persons with days off of school, daycare or work due to infections Total days Days per subject per year | 23 (39%) 93 1.7
Unscheduled Medical Visits due to infection Number of persons with unscheduled medical visits due to infections (%) Total visits Visits per subject per year | 24 (41%) 54 0.97
Hospitalization due to infection Number of subjects (%) Number of Days Hospitalizations per subject per year | 1 (1.7%) 5 0.02
SBI = serious bacterial infections.
aPerson-years: Person-time in years with 2 decimals = (the Final Clinical Visit Date - the Day 0 date+1) / 365.25, where the final clinical visit date is defined as the specimen collection date of the final clinical visit for urinalysis, or the specimen collection date for the clinical laboratory tests at the final clinical visit and Day 0 date is the start date of the first ASCENIV infusion.
b Defined as bacterial pneumonia, bacterial meningitis, bacteremia/septicemia, osteomyelitis/septic arthritis, and visceral abscess.
c The calculation of antibiotic use includes subjects who received antibiotics for therapeutic use.

15 REFERENCES

1. Gupta N, Ahmed I, Nissel-Horowitz S, Patel D, Mehrotra B. Intravenous gammaglobulin-associated acute renal failure. Am J Hematol 2001; 66:151-152.
2. Cayco, A.V., M.A. Perazella, and J.P. Hayslett. Renal insufficiency after intravenous immune globulin therapy: a report of two cases and an analysis of the literature. J Am Soc Nephrol 1997; 8:1788-1794.
3. Steinberger BA, Ford SM, Coleman TA. Intravenous immune globulin therapy results in post-infusional hyperproteinemia, increased serum viscosity, and pseudohyponatremia. Am J Hematol 2003; 73:97-100.
4. Dalakas MC. High-dose intravenous immunoglobulin and serum viscosity: risk of precipitating thromboembolic events. Neurology 1994; 44:223-226.
5. Woodruff RK, Grigg AP, Firkin FC, Smith IL. Fatal thrombotic events during treatment of autoimmune thrombocytopenia with intravenous immunoglobulin in elderly patients. Lancet 1986; 2:217-218.
6. Wolberg AS, Kon RH, Monroe DM, Hoffman M. Coagulation factor XI is a contaminant in intravenous immunoglobulin preparations. Am J Hematol 2000; 65:30-34.
7. Casteels-Van Daele, M., et al. Intravenous immune globulin and acute aseptic meningitis [letter]. N Engl J Med 1990; 323:614-615.
8. Kato, E., et al. Administration of immune globulin associated with aseptic meningitis [letter]. Jama 1988; 259:3269-3271.
9. Scribner, C.L., et al. Aseptic meningitis and intravenous immunoglobulin therapy [editorial, comment]. Ann Intern Med 1994; 121:305-306.
10. Copelan EA, Stohm PL, Kennedy MS, Tutschka PJ. Hemolysis following intravenous immune globulin therapy. Transfusion 1986; 26:410-412.
11. Thomas MJ, Misbah SA, Chapel HM, Jones M, Elrington G, Newsom-Davis J. Hemolysis after high-dose intravenous Ig. Blood 1993; 15:3789.
12. Wilson JR, Bhoopalam N, Fisher M. Hemolytic anemia associated with intravenous immunoglobulin. Muscle & Nerve 1997; 20:1142-1145.
13. Kessary-Shoham H, Levy Y, Shoenfeld Y, Lorber M, Gershon H. In vivo administration of intravenous immunoglobulin (IVIg) can lead to enhanced er ythrocyte sequestration. J Autoimmune 1999; 13:129-135.
14. Rizk A, Gorson KC, Kenney L, Weinstein R. Transfusion-related acute lung injury after the infusion of IVIG. Transfusion 2001; 41:264-268.
15. Siber GA, Werner BG, Halsey NA, et al. Interference of immune globulin with measles and rubella immunization. J Pediatr 1993; 122:204-211.
16. Salisbury D, Ramsay M, Noakes K, eds. Immunisation against infectious disease. The Stationery Office (TSO), London: UK Department of Health; 2009:426.
17. Hammarstrom L, Smith CIE. Placental transfer of intravenous immunoglobulin. Lancet 1986; 1:681.
18. Sidiropoulos D, Herrmann U, Morell A, von Muralt G, Barandun S. Transplacental passage of intravenous immunoglobulin in the last trimester of pregnancy. J Pediatr 1986; 109:505-508.

16 HOW SUPPLIED/STORAGE AND HANDLING

ASCENIV is supplied in a single-use, tamper-evident vial. The components used in the packaging for ASCENIV are not made with natural rubber latex. ASCENIV is supplied in 50 mL size containing 5 grams of protein (NDC 69800-0250-1).

- Store at 2 to 8°C (36 to 46°F) for up to 36 months from the date of manufacture. Do not freeze.
- Product may be stored up to 4 weeks at ≤ 25° C (77° F). After storage at room temperature product must be used or discarded.

17 PATIENT COUNSELING INFORMATION

Instruct patients taking ASCENIV to immediately report symptoms of:

- Thrombosis which includes pain and/or swelling of an arm or legs/feet with warmth over the affected area, discoloration of an arm or leg, unexplained shortness of breath, acute chest pain or discomfort that worsens on deep breathing, unexplained rapid pulse, numbness or weakness on one side of the body (see Warning and Precaution [5.2]).
- Acute Renal Dysfunction and Acute Renal Failure which includes decreased urine output, sudden weight gain, fluid retention/edema, and/or shortness of breath. Such symptoms may suggest kidney damage (see Boxed Warning, Warnings and Precautions [5.3]).
- Aseptic Meningitis Syndrome (AMS) which includes severe headache, neck stiffness, drowsiness, fever, sensitivity to light, painful eye movements, nausea and vomiting (see Warnings and Precautions [5.5]).
- Hemolysis which includes fatigue, increased heart rate, yellowing of skin or eyes, dark- colored urine (see Warnings and Precautions [5.5]).
- Transfusion-Related Acute Lung Injury (TRALI) which includes trouble breathing, chest pain, blue lips or extremities, fever (see Warnings and Precautions [5.7])

Inform patients that ASCENIV:

- Is made from human plasma and may contain infectious agents that can cause disease. While the risk that ASCENIV can transmit an infection has been reduced by screening plasma donors for prior exposure, testing donated plasma, and inactivating or removing certain viruses during manufacturing, patients should report any symptoms that concern them (see Description [11] and Warnings and Precautions [5]).
- Can interfere with their immune response to live viral vaccines (e.g., measles, mumps, rubella, and varicella). Instruct patients to notify their healthcare professional of this potential interaction when they are receiving vaccinations (see Drug Interactions [7]).

Manufactured by ADMA Biologics
Boca Raton, FL 33487 USA
U.S. License No. 2019
RM-5640 Rev.003